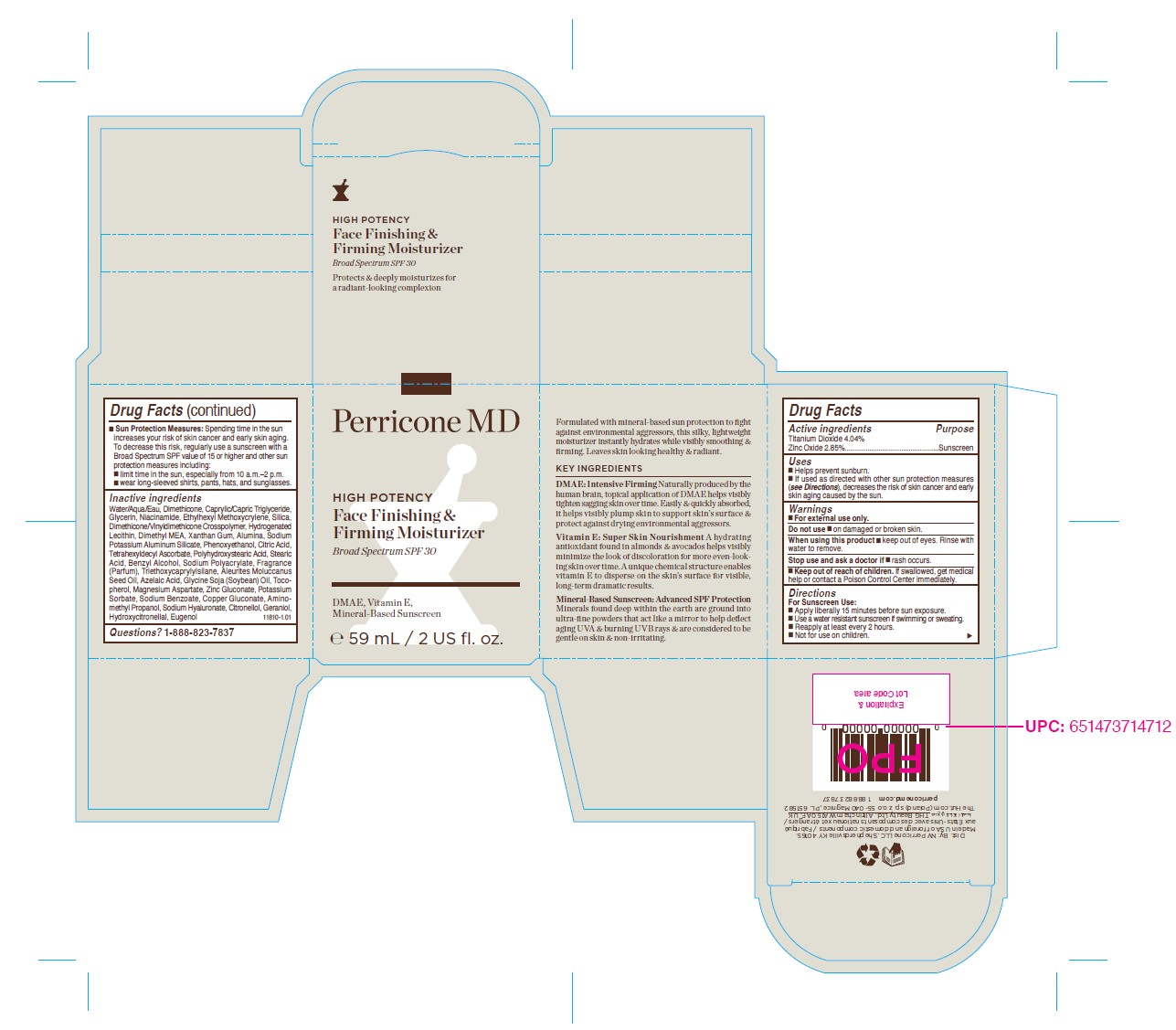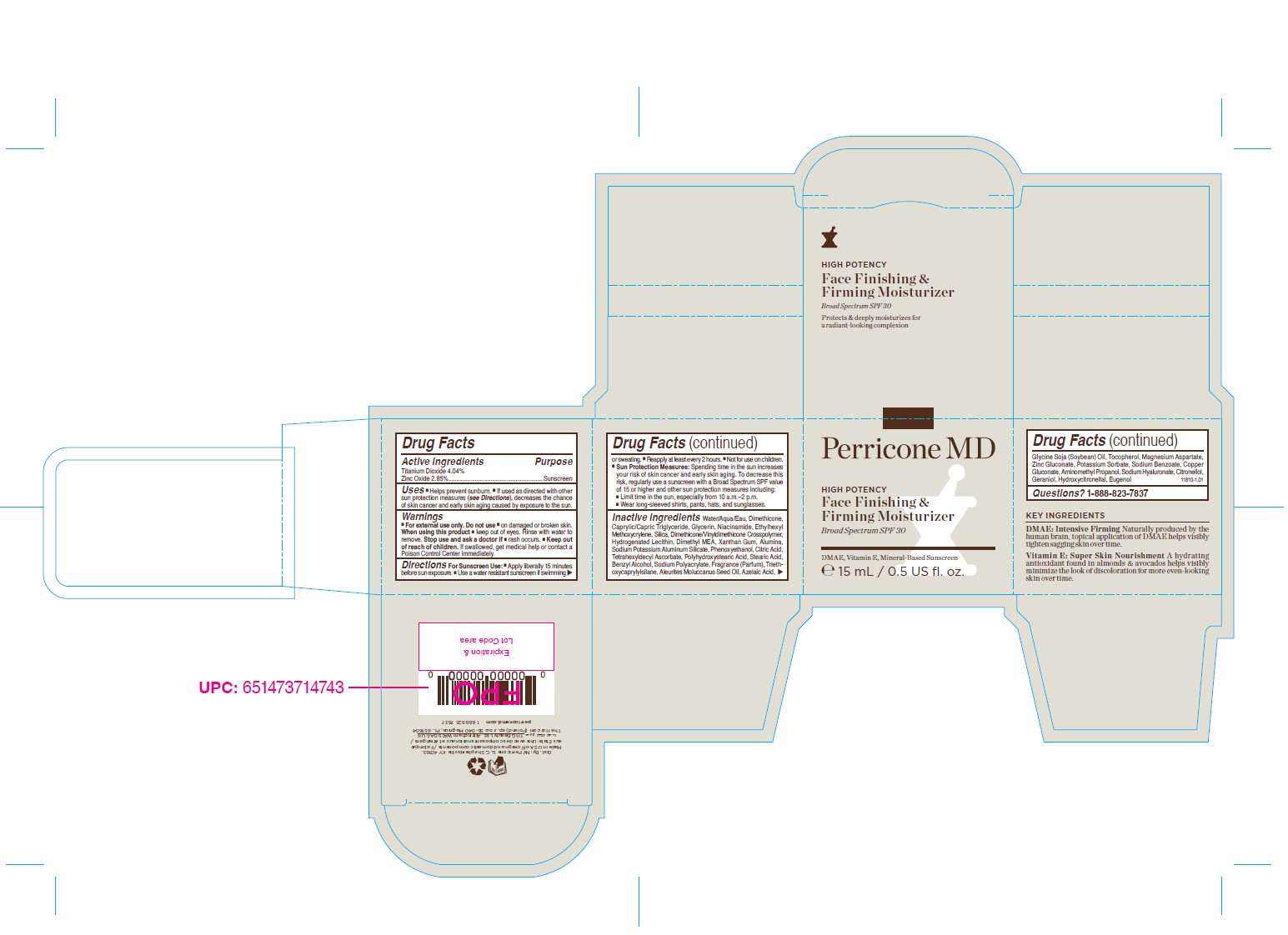 DRUG LABEL: Perricone High Potency Face Finishing and Firming Moisturizer
NDC: 84448-463 | Form: CREAM
Manufacturer: THG Beauty USA LLC
Category: otc | Type: HUMAN OTC DRUG LABEL
Date: 20251217

ACTIVE INGREDIENTS: TITANIUM DIOXIDE 4.04 g/59 mL; ZINC OXIDE 2.85 g/59 mL
INACTIVE INGREDIENTS: FRAGRANCE 13576; SODIUM POLYACRYLATE (2500000 MW); AZELAIC ACID; HYALURONATE SODIUM; EUGENOL; STEARIC ACID; POLYHYDROXYSTEARIC ACID (2300 MW); DIMETHICONE; MEDIUM-CHAIN TRIGLYCERIDES; GLYCERIN; HYDROGENATED SOYBEAN LECITHIN; NIACINAMIDE; ALUMINUM OXIDE; BENZYL ALCOHOL; ETHYLHEXYL METHOXYCRYLENE; DIMETHICONE CROSSPOLYMER; DEANOL; XANTHAN GUM; PHENOXYETHANOL; CITRIC ACID MONOHYDRATE; TETRAHEXYLDECYL ASCORBATE; .ALPHA.-TOCOPHEROL, D-; GERANIOL; COPPER GLUCONATE; TRIETHOXYCAPRYLYLSILANE; MAGNESIUM ASPARTATE; AMINOMETHYLPROPANOL; WATER; KUKUI NUT OIL; POTASSIUM SORBATE; .BETA.-CITRONELLOL, (R)-; SODIUM POTASSIUM ALUMINUM SILICATE; ZINC GLUCONATE; SODIUM BENZOATE; HYDROXYCITRONELLAL; SILICON DIOXIDE; SOYBEAN OIL

ACTIVE INGREDIENT

Titanium Dioxide - 4.04%

Zinc Oxide - 2.85%

PURPOSE

Sunscreen

DOSAGE AND ADMINISTRATION

- Apply generously 15 minutes before sun exposure.
- Use a water-resistant sunscreen if swimming or sweating.
- Reapply at least every 2 hours.
- Not for use on children
- Sun Protection Measures: Spending time in the sun increases your risk of skin cancer and early skin aging. To decrease this risk, regularly use a sunscreen with a Broad Spectrum value of SPF 15 or higher and other sun protection measures including:
  - Limit time in the sun, especially from 10 a.m.- 2 p.m.
  - wear long-sleeved shirts, pants, hats and sunglasses.

INACTIVE INGREDIENT

Water/Aqua/Eau, Dimethicone, Caprylic/Capric Triglyceride, Glycerin, Niacinamide, Ethylhexyl Methoxycrylene, Silica, Dimethicone/Vinyldimethicone Crosspolymer, Hydrogenated Lecithin, Dimethyl MEA, Xanthan Gum, Alumina, Sodium Potassium Aluminum Silicate, Phenoxyethanol, Citric Acid, Tetrahexyldecyl Ascorbate, Polyhydroxystearic Acid, Stearic Acid, Benzyl Alcohol, Sodium Polyacrylate, Fragrance (Parfum), Triethoxycaprylylsilane, Aleurites Moluccanus Seed Oil, Azelaic Acid, Glycine Soja (Soybean) Oil, Tocopherol, Magnesium Aspartate, Zinc Gluconate, Potassium Sorbate, Sodium Benzoate, Sodium Hyaluronate, Copper Gluconate, Aminomethyl Propanol, Citronellol, Geraniol, Hydroxycitronellal, Eugenol

INDICATIONS AND USAGE

- Helps prevent sunburn
- If used as directed with other sun protection measures (see Directions), decreases the risk of skin cancer and early skin aging caused by the sun.

WARNINGS

For external use only.

DO NOT USE

on damaged or broken skin.

WHEN USING

keep out of eyes. Rinse with water to remove.

STOP USE

if rash occurs.

KEEP OUT OF REACH OF CHILDREN

If swallowed, get medical help or contact a Poison Control Centre right away.

QUESTIONS

1-888-823-7837